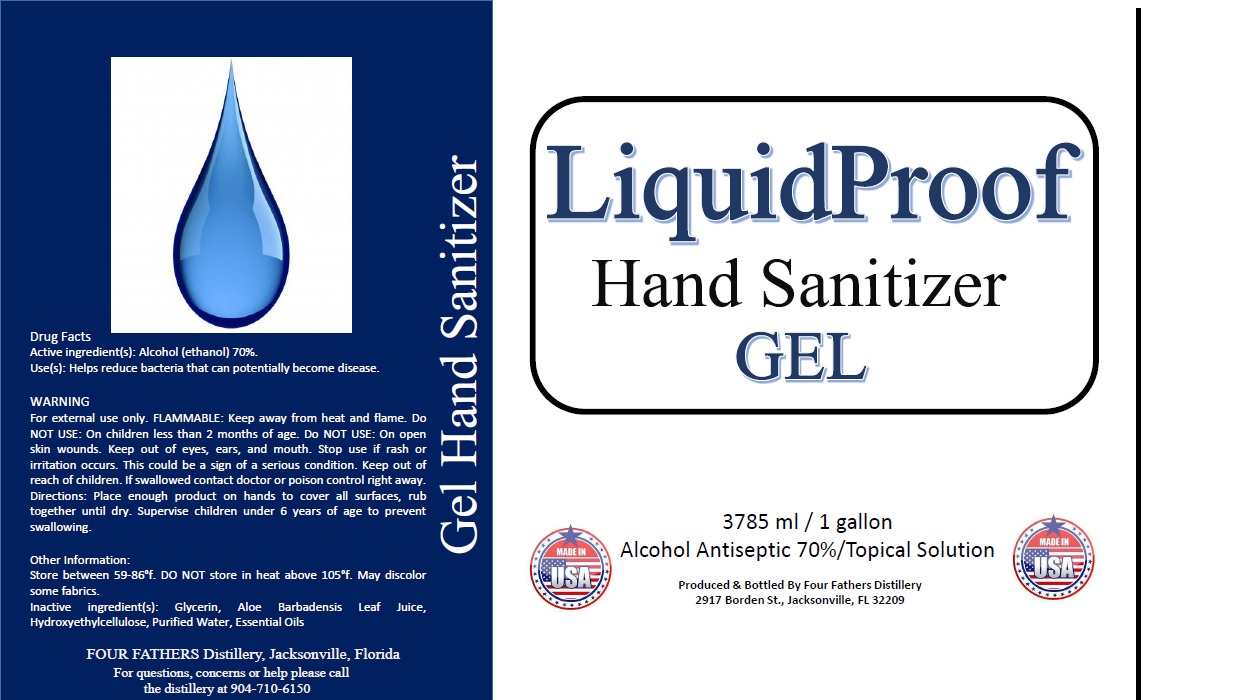 DRUG LABEL: LiquidProof
NDC: 78829-500 | Form: GEL
Manufacturer: Four Fathers Distillery LLC
Category: otc | Type: HUMAN OTC DRUG LABEL
Date: 20201002

ACTIVE INGREDIENTS: ALCOHOL 70 mL/100 mL
INACTIVE INGREDIENTS: GLYCERIN; ALOE VERA LEAF; HYDROXYETHYL CELLULOSE, UNSPECIFIED; WATER; PEPPERMINT OIL; EUCALYPTUS OIL

LiquidProof Hand Sanitizer GEL

Active ingredient(s): Alcohol (ethanol) 70%.

Purpose Antiseptic

INDICATIONS AND USAGE

Use(s): Helps reduce bacteria that can potentially become disease.

WARNING

For external use only. FLAMMABLE: Keep away from heat and flame. DO NOT USE: On children less than 2 months of age. DO NOT USE: On open skin wounds. Keep out of eyes, ears, and mouth. Stop use if rash or irritation occurs. This could be a sign of a serious condition.

Keep out of reach of children. If swallowed contact doctor or poison control right away.

DOSAGE AND ADMINISTRATION

Directions: Place enough product on hands to cover all surfaces, rub together until dry. Supervise children under 6 years of age to prevent swallowing.

Other Information:

Store between 59-86°f. DO NOT store in heat above 105°f. May discolor some fabrics

Inactive ingredient(s): Glycerin, Aloe Barbadensis Leaf Juice, Hydroxyethylcellulose, Purified Water, Essential Oils

Alcohol Antiseptic 70%/Topical Solution

MADE IN USA

Produced & Bottled By Four Fathers Distillery

2917 Borden St., Jacksonville, FL 32209

FOUR FATHERS Distillery, Jacksonville, Florida

For questions, concerns or help please call the distillery at 904-710-6150